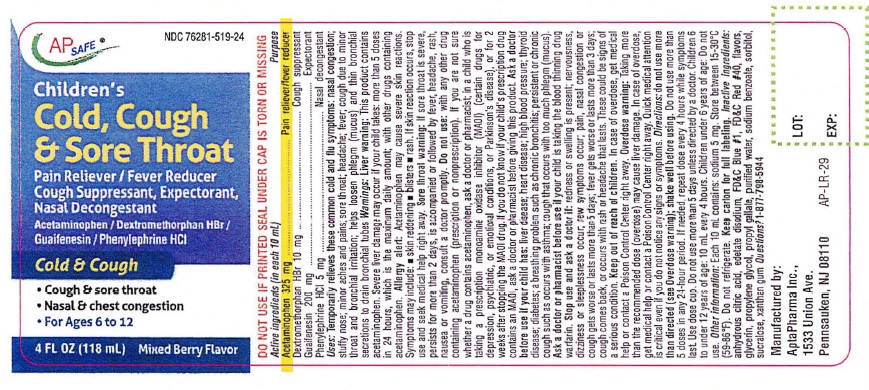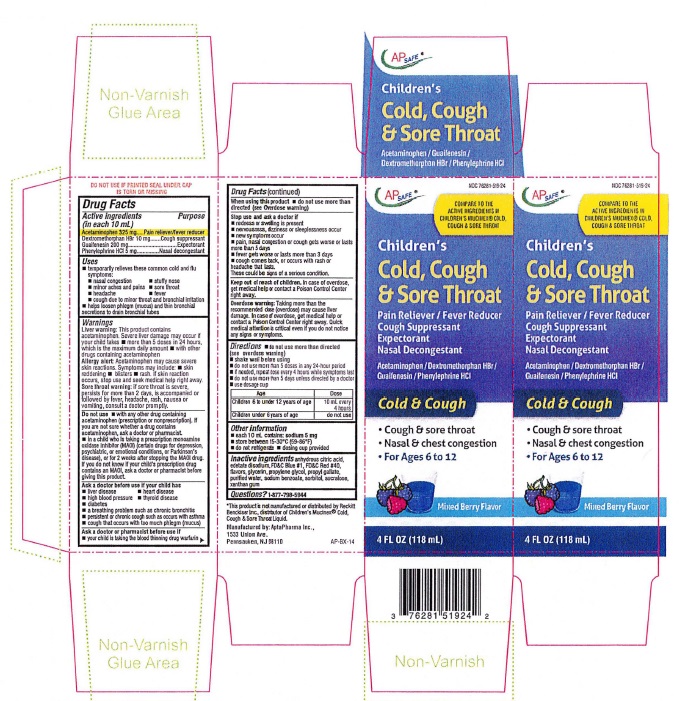 DRUG LABEL: CHILDRENS COLD COUGH and SORE THROAT MIXED BERRY
NDC: 76281-519 | Form: LIQUID
Manufacturer: AptaPharma Inc.
Category: otc | Type: HUMAN OTC DRUG LABEL
Date: 20240201

ACTIVE INGREDIENTS: ACETAMINOPHEN 325 mg/10 mL; DEXTROMETHORPHAN HYDROBROMIDE 10 mg/10 mL; GUAIFENESIN 200 mg/10 mL; PHENYLEPHRINE HYDROCHLORIDE 5 mg/10 mL
INACTIVE INGREDIENTS: ANHYDROUS CITRIC ACID; EDETATE DISODIUM; FD&C BLUE NO. 1; FD&C RED NO. 40; GLYCERIN; PROPYLENE GLYCOL; PROPYL GALLATE; WATER; SODIUM BENZOATE; SORBITOL; SUCRALOSE; XANTHAN GUM

Children's Cold, Cough & Sore Throat mixed Berry Flavor

Drug Facts

Active ingredients Purpose
(in each 10 mL)
Acetaminophen 325 mg
Dextromethorphan HBr 10 mg
Guaifenesin 200 mg
Phenylephrine HCl 5 mg

Purpose

Acetaminophen ……....…….... Pain reliever/fever reducer
Dextromethorphan HBr …....Cough suppressant
Guaifenesin ………….....…..…. Expectorant
Phenylephrine HCI …...……….Nasal decongestant

Uses
• temporarily relieves these common cold and flu symptoms:
• nasal congestion • stuffy nose • minor aches and pains • sore throat • headache • fever
• cough due to minor throat and bronchial irritation
• helps loosen phlegm (mucus) and thin bronchial secretions to drain bronchial tube

Warnings

Liver warning: This product contains acetaminophen. Severe liver damage may occur if your child takes
• more than 5 doses in 24 hours, which is the maximum daily amount
• with other drugs containing acetaminophen

Allergy alert: Acetaminophen may cause severe skin reactions. Symptoms may include • skinreddening • blisters • rash. If skin reaction occurs, stop use and seek medical help right away.

Sore throat warning: if sore throat is severe, persists for more than 2 days, is accompanied or followed by fever, headache, rash, nausea or vomiting, consult a doctor promptly.

Do not use • with any other drug containing acetaminophen (prescription or nonprescription). If you are not sure whether a drug contains acetaminophen, ask a doctor or pharmacist. • in a child who is taking a prescription monoamine oxidase inhibitor (MAOI) (certain drugs for depression, psychiatric, or emotional conditions, or Parkinson's disease), or for 2 weeks after stopping the MAOI drug. If you do not know if your child's prescription drug contains an MAOI, ask a doctor or pharmacist before giving this product.

Ask a doctor before use if your child has
• Iiver disease • heart disease • high blood pressure • thyroid disease • diabetes • a breathing problem such as chronic bronchitis • persistent or chronic cough such as occurs with asthma • cough that occurs with too much phlegm (mucus)

Ask a doctor or pharmacist before use if • your child is taking the blood thinning drug warfarin.

When using this product • do not use more than directed (see Overdose warning)

Stop use and ask a doctor if
• redness or swelling is present
• nervousness, dizziness or sleeplessness occur
• new symptoms occur
• pain, nasal congestion or cough gets worse or lasts more than 5 days
• fever gets worse or lasts more than 3 days
• cough comes back, or occurs with rash or headache that lasts.
These could be signs of a serious condition.

Keep out of reach of children. In case of overdose, get
medical help or contact a Poison Control Center right
away.

OVERDOSAGE

Overdose warning
Taking more than the recommended dose (overdose) may cause liver damage. In case of overdose, get medical help or
contact a Poison Control Center right away. Quick medical attention is critical for adults as well as for children even if
you do not notice any signs or symptoms.

Directions
• do not use more than directed (see Overdose warning)
• shake well before using
• do not use more than 5 doses in any 24-hour period
• if needed, repeat dose every 4 hours while symptoms last
• do not use more than 5 days unless directed by a doctor
• use dosage cup

Age Dose
Children 6 to under 12 years of age | 10 mL every 4 hours
Children under 6 years of age | Do not use

Other information
• each 10 mL contains: sodium 5 mg
• store between IS-30°C (59-86°F)
• do not refrigerate
• dosage cup provided

Inactive ingredients
anhydrous citric acid, edetate disodium, FD&C Blue #1, FD&C Red #40, flavors, glycerin, propylene glycol, propyl gallate,
purified water, sodium benzoate, sorbitol, sucralose, Xanthan gum

QUESTIONS

Questions? Call weekdays from 9:30AM to 4:30 PM EST 1-877-798-5944

Maximum Strength MAX COLD & SINUS

AP SAFE NDC 76281-519-24

Compare to Mucinex® FAST-MAX™ Cold & Sinus
Active ingredients*
Children's

Cold, Cough

& Sore Throat

Pain reliever/Fever Reducer
Cough Suppresant
Expectorant
Nasal decongestant

For Ages 6 to 12

Mixed Berry Flavor

4 FL OZ (118 mL)

DO NOT USE IF PRINTED SEAL UNDER CAP IS TORN OR MISSING

Manufactured by:
AptaPharma Inc.,
1533 Union Ave.
Pennsauken, NJ 08110

* This product is not manufactured or distributed by Reckitt

Benckiser Inc., distributor ofchildren's Mucinex® Cold,

Cough & Sore Throat liquid.

res